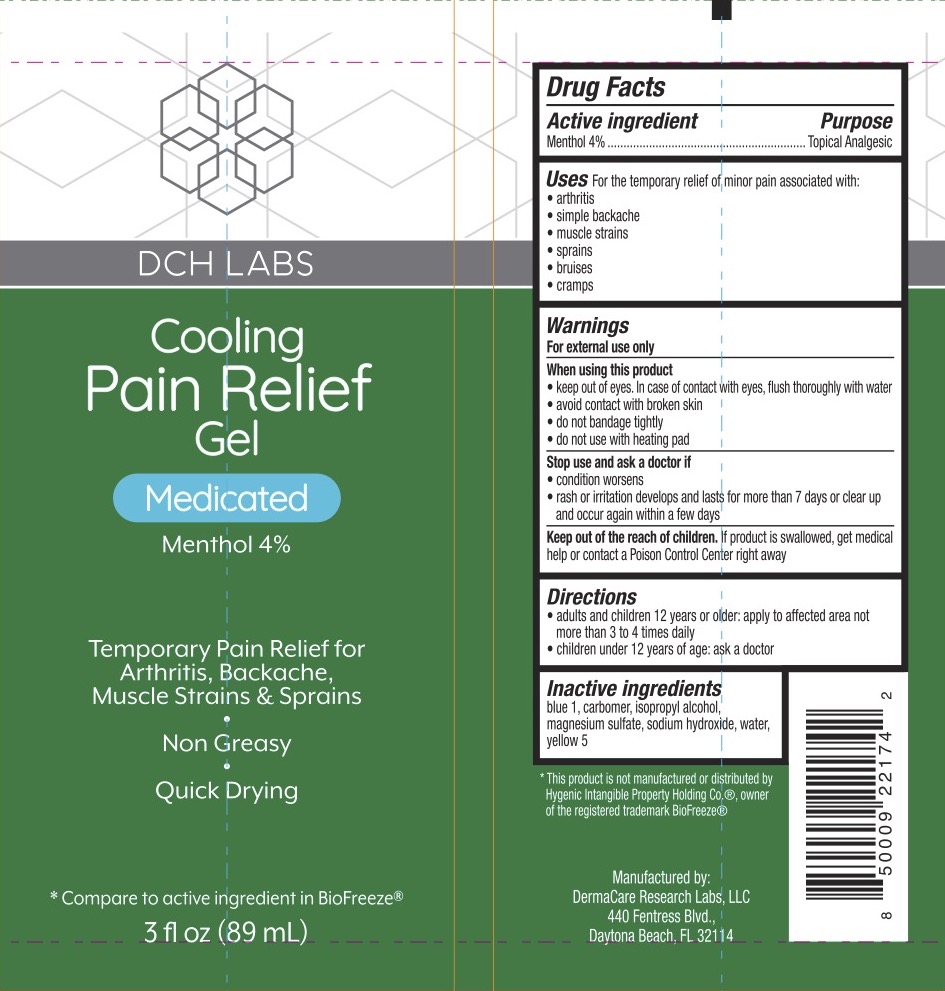 DRUG LABEL: DCH Cooling Pain Relief
NDC: 72839-297 | Form: GEL
Manufacturer: Derma Care Research Labs, LLC
Category: otc | Type: HUMAN OTC DRUG LABEL
Date: 20241219

ACTIVE INGREDIENTS: MENTHOL 4 g/100 mL
INACTIVE INGREDIENTS: FD&C BLUE NO. 1; CARBOMER INTERPOLYMER TYPE B (ALLYL PENTAERYTHRITOL CROSSLINKED); WATER; MAGNESIUM SULFATE, UNSPECIFIED FORM; ISOPROPYL ALCOHOL; FD&C YELLOW NO. 5; SODIUM HYDROXIDE

DCH Cooling Pain Relief Gel, Menthol 4%

ACTIVE INGREDIENT

Menthol 4%

PURPOSE

Topical Analgesic

INDICATIONS AND USAGE

For the temporary relief of minor aches and pains associated with arthritis, simple backache, strains, sprains, and bruises.

WARNINGS

For external use only.

When using this product keep out of eyes. In case of contact with eyes, flush thoroughly with water. Avoid contact with broken skin, do not bandage tightly, and do not use with heating pad.

Stop use and ask a doctor if condition worsens, symptoms last more than 7 days or clear and occur again within a few days.

KEEP OUT OF REACH OF CHILDREN

If product is swallowed, get medical help or contact a Poison Control Center right away.

DOSAGE AND ADMINISTRATION

• adults and children 12 years and older, apply to affected area not more than 3 to 4 times daily. • Children under 12 years old, ask a doctor

INACTIVE INGREDIENT

Blue 1, carbomer, isopropyl alcohol, magnesium sulfate, sodium hydroxide, water, yellow 5.